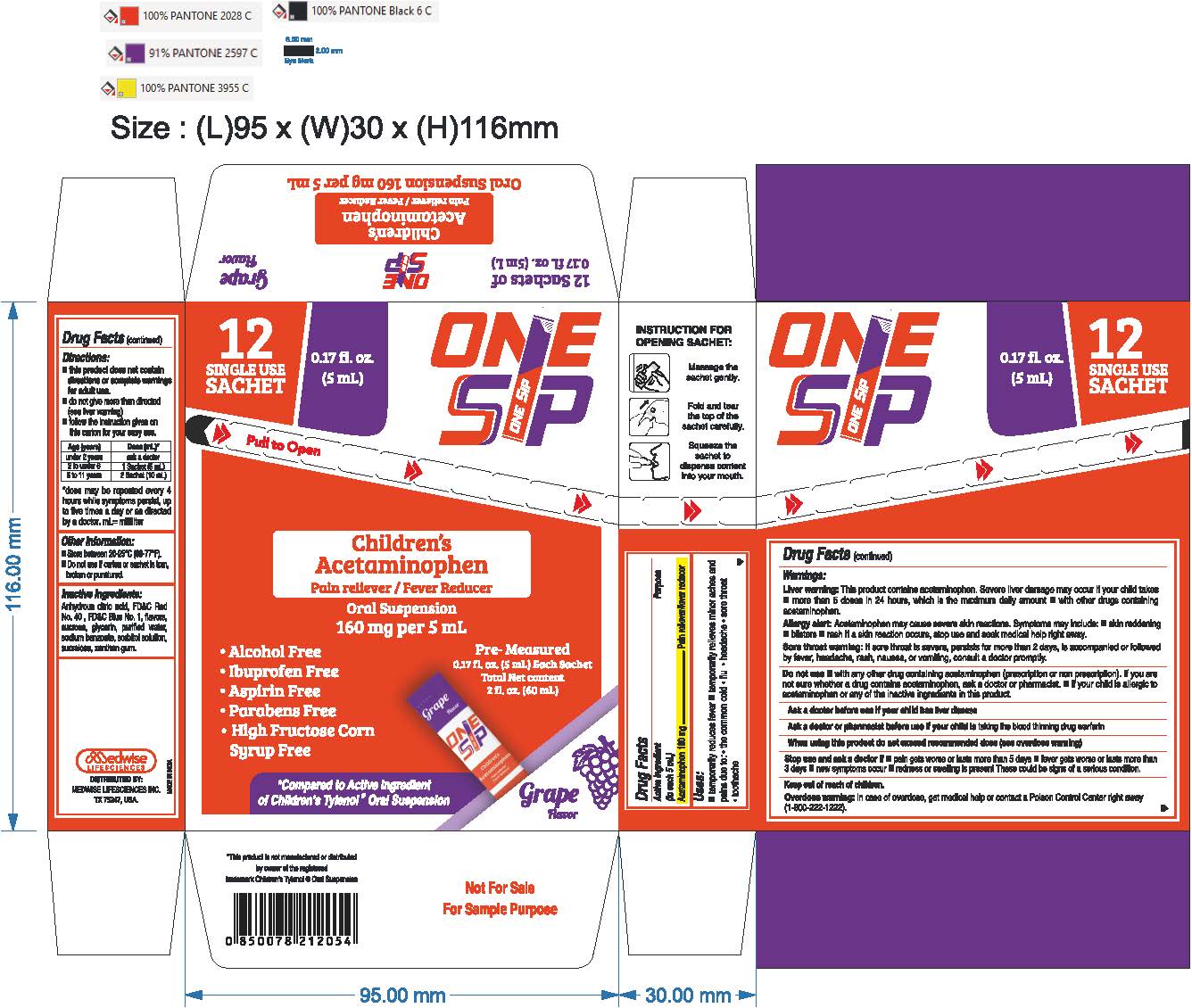 DRUG LABEL: OneSsip Acetaminophen
NDC: 87078-131 | Form: SUSPENSION
Manufacturer: MEDWISE LIFESCIENCES INC.
Category: otc | Type: HUMAN OTC DRUG LABEL
Date: 20251112

ACTIVE INGREDIENTS: ACETAMINOPHEN 160 mg/5 mL
INACTIVE INGREDIENTS: GLYCERIN; WATER; SORBITOL SOLUTION 70%; FD&C RED NO. 40; SUCROSE; XANTHAN GUM; SUCRALOSE; ANHYDROUS CITRIC ACID; FD&C BLUE NO. 1; SODIUM BENZOATE

Acetaminophen Oral Suspension 160 mg per 5 mL (Grape Flavor)
Drug Facts

Active ingredient (in each 5 mL)

Acetaminophen 160 mg

Purpose

Pain reliever/fever reducer

Uses

- Temporarily reduces fever
- Temporarily relieves minor aches and pains due to:
  - the common cold
  - flu
  - headache
  - sore throat
  - toothache

Warnings

Liver warning

This product contains acetaminophen. Severe liver damage may occur if your child takes

- more than 5 doses in 24 hours, which is the maximum daily amount
- with other drugs containing acetaminophen

Allergy alert: Acetaminophen may cause severe skin reactions. Symptoms may include:

- skin reddening
- blisters
- rash

If a skin reaction occurs, stop use and seek medical help right away.

Sore throat warning: if sore throat is severe, persists for more than 2 days, is accompanied or followed by fever, headache, rash, nausea, or vomiting, consult a doctor promptly.

Do not use

- with any other drug containing acetaminophen (prescription or nonprescription). If you are not sure whether a drug contains acetaminophen, ask a doctor or pharmacist.
- if your child is allergic to acetaminophen or any of the inactive ingredients in this product

Ask a doctor before use if your child has liver disease

Ask a doctor or pharmacist before use if your child is taking the blood thinning drug warfarin.

When using this product do not exceed recommended dose (see overdose warning)

Stop use and ask a doctor if

- pain gets worse or lasts more than 5 days
- fever gets worse or lasts more than 3 days
- new symptoms occur
- redness or swelling is present

These could be signs of a serious condition.

Keep out of reach of children.

OVERDOSAGE

Overdose warning

In case of overdose, get medical help or contact a Poison Control Center right away. (1-800-222-1222)

Directions

- this product does not contain directions or complete warnings for adult use.
- do not give more than directed (see overdose warning)
- Follow the instruction given on this carton for your easy use.

Age (Years) | Dose (mL)*
under 2 years | ask a doctor
2 to under 6 | 1 Sachet (5 mL)
6 to 11 years | 2 Sachet (10 mL)

*dose may be repeated every 4 hours while symptoms persist, upto five times a day or as directed by a doctor.

mL = mililiter

Other information

- store between 20-25°C (68-77°F)
- do not use if carton or sachet is torn, broken or punctured.

Inactive ingredients

anhydrous citric acid, FD&C Red No. 40, FD&C Blue 1, flavors, glycerin, purified water, sodium benzoate, sorbitol solution, sucralose, sucrose, xanthan gum

Questions or comments?

call 1-516-675-8915

PACKAGE LABEL

OneSsip Acetaminophen 160 mg per 5 mL Cherry Flavor Oral Suspension

Free of:

- Dyes
- Alcohol
- Ibuprofen
- Aspirin
- Parabens
- High Fructose Corn Syrup